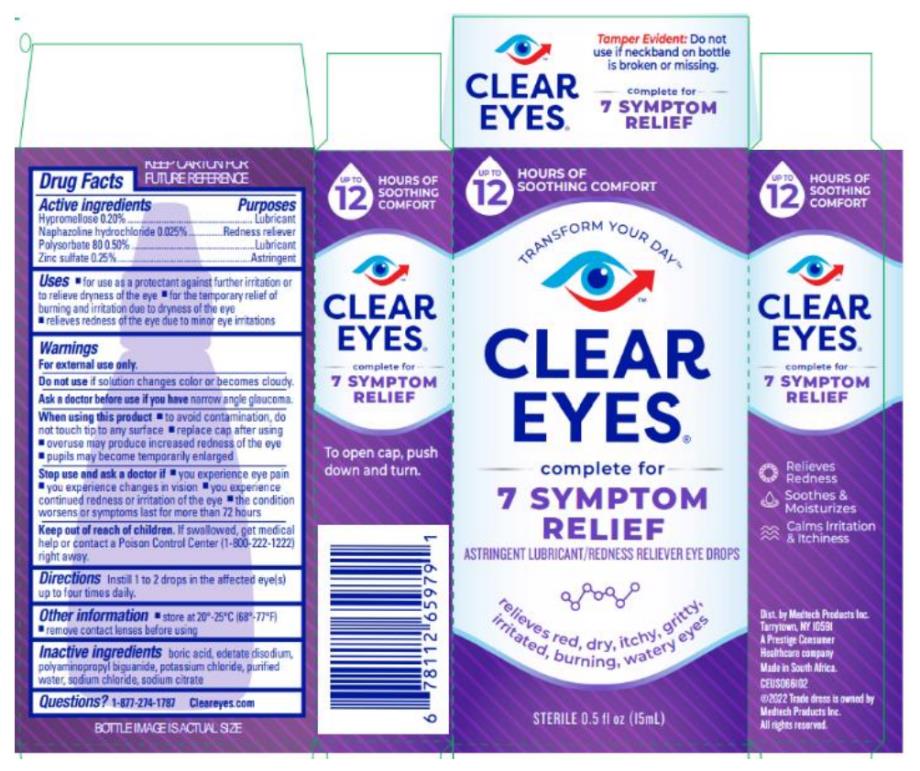 DRUG LABEL: Clear Eyes Complete 7 Sympton Relief
NDC: 67172-707 | Form: LIQUID
Manufacturer: Prestige Brands Holdings, Inc.
Category: otc | Type: HUMAN OTC DRUG LABEL
Date: 20241025

ACTIVE INGREDIENTS: HYPROMELLOSES .5 mg/1 mL; NAPHAZOLINE HYDROCHLORIDE .0625 mg/1 mL; POLYSORBATE 80 1.25 mg/1 mL; ZINC SULFATE .625 mg/1 mL
INACTIVE INGREDIENTS: BORIC ACID; EDETATE DISODIUM; POTASSIUM CHLORIDE; SODIUM CHLORIDE; SODIUM CITRATE

Clear Eyes Complete 7 Symptom Relief

Drug Facts

Active Ingredients

Hypromellose 0.20%

Purpose

Lubricant

Active Ingredients

Naphazoline Hydrochloride 0.025%

Purpose

Redness Reliever

Active Ingredients

Polysorbate 80 0.50%

Purpose

Lubricant

Active Ingredients

Zinc Sulfate 0.25%

Purpose

Lubricant

Uses

- For use as a protectant against further irritation or to relieve dryness of the eye.
- For the temporary relief of burning & irritation due to the dryness of the eye.
- Relieves redness of the eye due to minor eye irritations.

Warnings

For external use only.

Do not use

if solution changes color or becomes cloudy.

Ask a doctor before use

if you have narrow angle glaucoma

When using this product:

- To avoid contamination, do not touch tip of container to any surface.
- Replace cap after using.
- Overuse of this product may produce increased redness of the eye.
- Pupils may become enlarged temporarily.

Stop use & ask a doctor if:

- you experience eye pain
- you experience changes in vision
- you experience continued redness or irritation of the eye
- the condition worsens
- symptoms last for more than 72 hours

Keep out of reach of children.

If swallowed, get medical help or contact a Poison Control Center right away.

Directions

Instill 1 to 2 drops in the affected eye(s) up to four times daily.

Other Information

- Store at room temperature.
- Remove contact lenses before using.
- Tamper Evident: Do not use if neckband on bottle is broken or missing.

Inactive Ingredients

calcium chloride, citric acid, edetate disodium, magnesium chloride, potassium chloride, purified water, sodium citrate, sodium chloride and sorbic acid.

Questions?

1-877-274-1787

www.cleareyes.com

PRINCIPAL DISPLAY PANEL

CLEAR
EYES ®
complete for
7 SYMPTOM RELIEF
ASTRINGENT LUBRICANT/REDNESS RELIEVER EYE DROPS
Sterile 0.5 FL oz (15 mL)